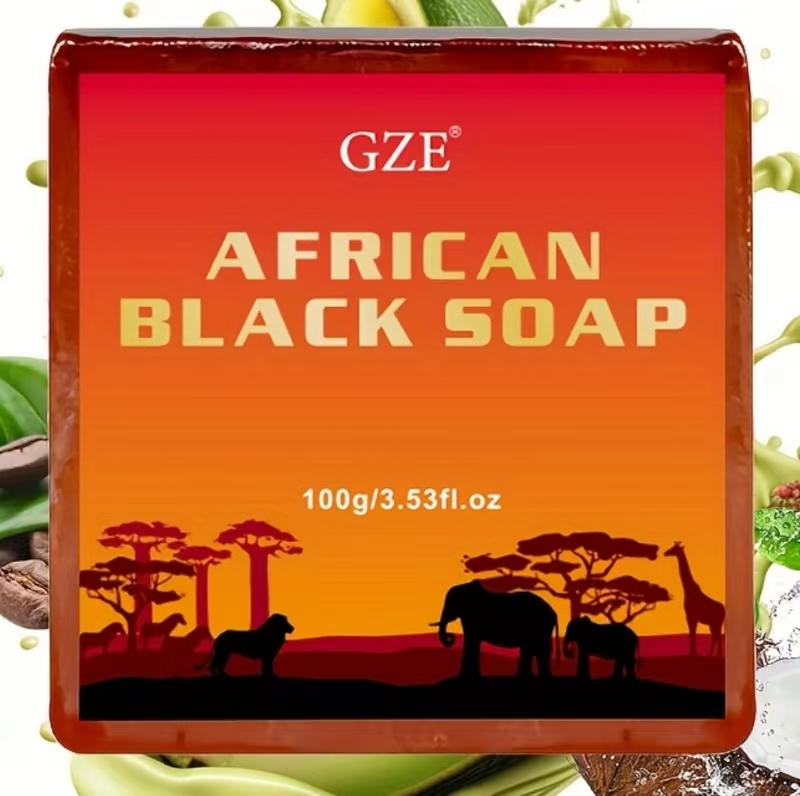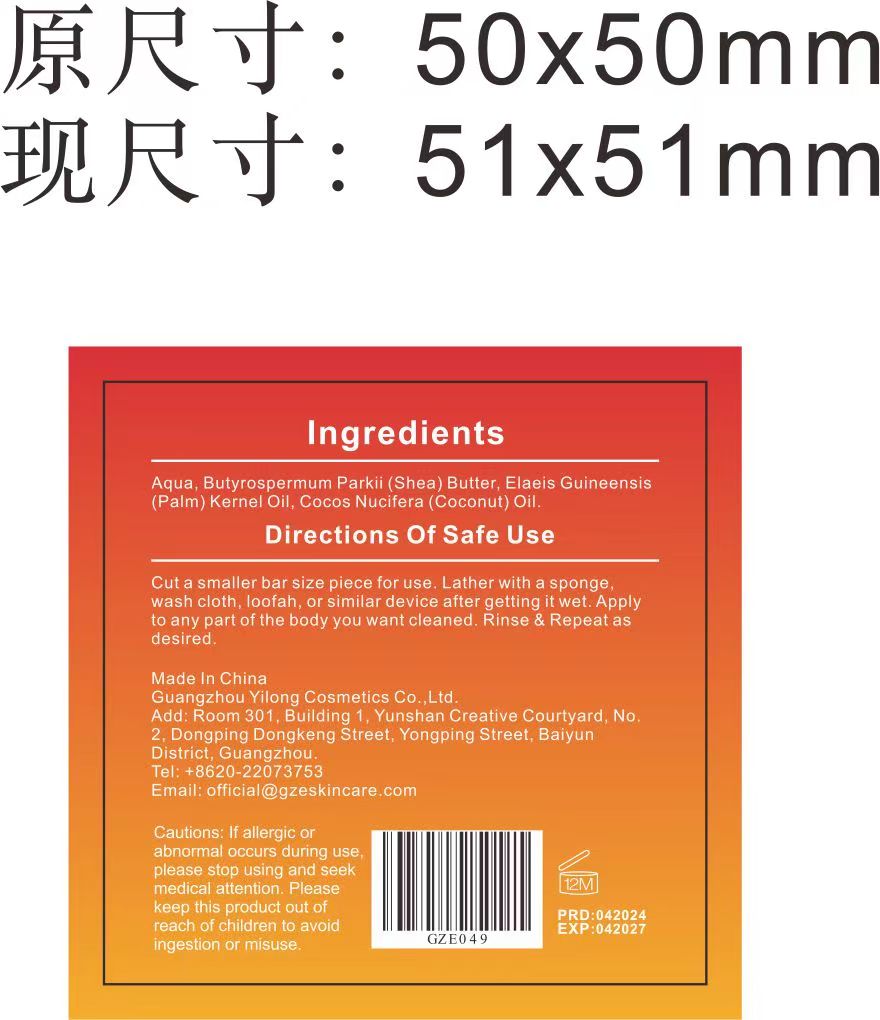 DRUG LABEL: GZE African BlackSoap
NDC: 83566-049 | Form: SOAP
Manufacturer: Guangzhou Yilong Cosmetics Co., Ltd
Category: otc | Type: HUMAN OTC DRUG LABEL
Date: 20240622

ACTIVE INGREDIENTS: BUTYROSPERMUM PARKII (SHEA) BUTTER UNSAPONIFIABLES 30 g/100 g
INACTIVE INGREDIENTS: COCONUT OIL; WATER; ELAEIS GUINEENSIS FRUIT BUTTER

GZE African BlackSoap

PURPOSE

Cleaning skin.

INDICATIONS AND USAGE

Cut a smaller bar size piece for use. Lather with a sponge,wash cloth, loofah, or similar device after getting it wet. Applto any part of the body you want cleaned. Rinse & Repeat asdesired.

WARNINGS

For external use only.

Stop use and ask a doctor if rash occurs.

Do not use on damaged or broken skin.

When using this product keep out of eyes. Rinse with water to remove.

Keep out of reach of children. If swallowed, get medical help or contact a Poison Control Center right away.

DOSAGE AND ADMINISTRATION

Cut a smaller bar size piece for use. Lather with a spongewash cloth, loofah, or similar device after getting it wet. Applto any part of the body you want cleaned. Rinse & Repeat asdesired.

ACTIVE INGREDIENT

BUTYROSPERMUM PARKII (SHEA) BUTTER UNSAPONIFIABLES

INACTIVE INGREDIENT

Water

Elaeis Guineensis (Palm) Kernel Oil

Cocos Nucifera(Coconut) Oil